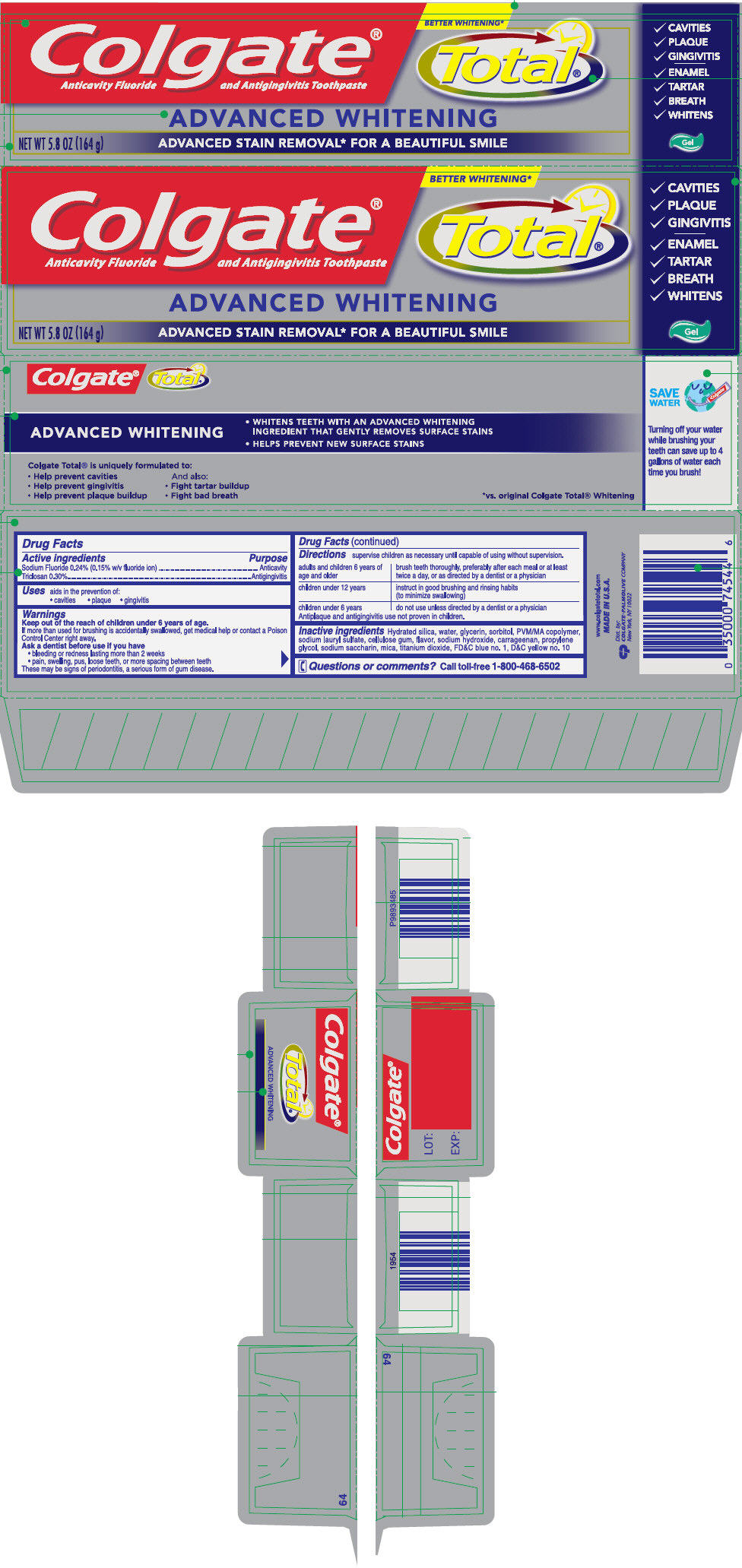 DRUG LABEL: Colgate Total Advanced Whitening
NDC: 67659-360 | Form: PASTE, DENTIFRICE
Manufacturer: Team Technologies, Inc
Category: otc | Type: HUMAN OTC DRUG LABEL
Date: 20160520

ACTIVE INGREDIENTS: SODIUM FLUORIDE 2.4 mg/1 g; TRICLOSAN 3 mg/1 g
INACTIVE INGREDIENTS: WATER; HYDRATED SILICA; GLYCERIN; SORBITOL; BUTYL ESTER OF METHYL VINYL ETHER/MALEIC ANHYDRIDE COPOLYMER (125000 MW); SODIUM LAURYL SULFATE; SODIUM HYDROXIDE; PROPYLENE GLYCOL; SACCHARIN SODIUM; CARBOXYMETHYLCELLULOSE SODIUM, UNSPECIFIED FORM; MICA; TITANIUM DIOXIDE; CARRAGEENAN; FD&C BLUE NO. 1; D&C YELLOW NO. 10

Colgate® Total® Advanced Whitening Gel

Drug Facts

ACTIVE INGREDIENT

Active ingredients | Purpose
Sodium Fluoride 0.24% (0.15% w/v fluoride ion) | Anticavity
Triclosan 0.30% | Antigingivitis

Uses

aids in the prevention of:

- cavities
- plaque
- gingivitis

Warnings

KEEP OUT OF REACH OF CHILDREN

Keep out of the reach of children under 6 years of age.

If more than used for brushing is accidentally swallowed, get medical help or contact a Poison Control Center right away.

Ask a dentist before use if you have

- bleeding or redness lasting more than 2 weeks
- pain, swelling, pus, loose teeth, or more spacing between teeth

These may be signs of periodontitis, a serious form of gum disease.

Directions

supervise children as necessary until capable of using without supervision.

adults and children 6 years of age and older | brush teeth thoroughly, preferably after each meal or at least twice a day, or as directed by a dentist or a physician
children under 12 years | instruct in good brushing and rinsing habits (to minimize swallowing)
children under 6 years | do not use unless directed by a dentist or a physician

Antiplaque and antigingivitis use not proven in children.

Inactive ingredients

Hydrated silica, water, glycerin, sorbitol, PVM/MA copolymer, sodium lauryl sulfate, cellulose gum, flavor, sodium hydroxide, carrageenan, propylene glycol, sodium saccharin, mica, titanium dioxide, FD&C blue no. 1, D&C yellow no. 10

Questions or comments?

Call toll-free 1-800-468-6502

Dist. by:
COLGATE-PALMOLIVE COMPANY
New York, NY 10022

PRINCIPAL DISPLAY PANEL - 164 g Tube Carton

BETTER WHITENING*

Colgate®
Anticavity Fluoride and Antigingivitis Toothpaste

Total®

ADVANCED WHITENING

NET WT 5.8 OZ (164 g)
ADVANCED STAIN REMOVAL* FOR A BEAUTIFUL SMILE

✓ CAVITIES
✓ PLAQUE
✓ GINGIVITIS
✓ ENAMEL
✓ TARTAR
✓ BREATH
✓ WHITENS

Gel